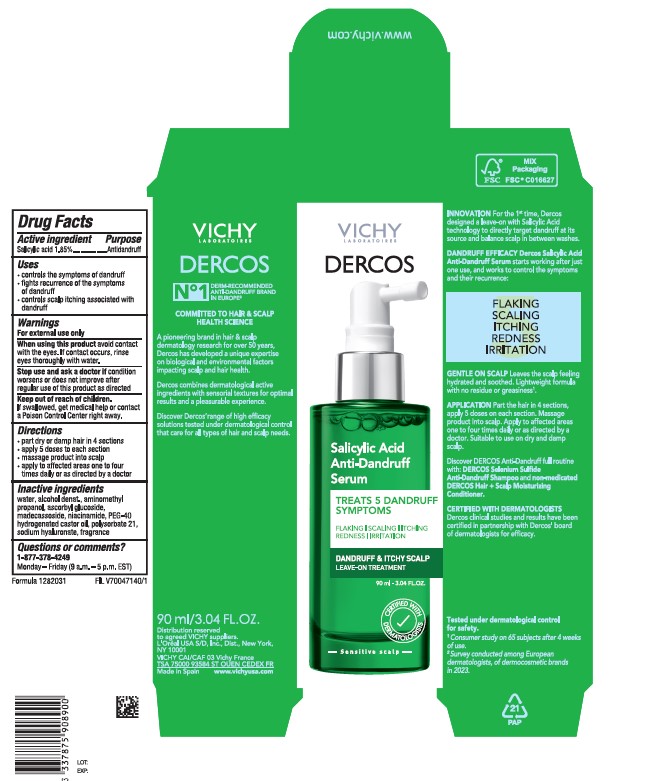 DRUG LABEL: Dercos Salicylic Acid Anti-Dandruff Serum
NDC: 49967-892 | Form: LIQUID
Manufacturer: L'Oreal USA Products Inc
Category: otc | Type: HUMAN OTC DRUG LABEL
Date: 20241107

ACTIVE INGREDIENTS: SALICYLIC ACID 18.5 mg/1 mL
INACTIVE INGREDIENTS: WATER; ALCOHOL; AMINOMETHYLPROPANOL; ASCORBYL GLUCOSIDE; MADECASSOSIDE; NIACINAMIDE; POLYOXYL 40 HYDROGENATED CASTOR OIL; POLYSORBATE 21; HYALURONATE SODIUM

Drug Facts

Active ingredient

Salicylic acid 1.85%

Purpose

Antidandruff

Uses

- controls the symptoms of dandruff
- fights recurrence of the symptoms of dandruff
- controls scalp itching associated with dandruff

Warnings

For external use only

When using this product

Avoid contact with the eyes. If contact occurs, rinse eyes thoroughly with water.

Stop use and ask a doctor if

condition worsens or does not improve after regular use of this product as directed

Keep out of reach of children.

If swallowed, get medical help or contact a Poison Control Center right away.

Directions

- part dry or damp hair in 4 sections
- apply 5 doses to each section
- massage product into scalp
- apply to affected areas one to four times daily or as directed by a doctor

Inactive ingredients

water, alcohol denat., aminomethyl propanol, ascorbyl glucoside, madecassoside, niacinamide, PEG-40 hydrogenated castor oil, polysorbate 21, sodium hyaluronate, fragrance

Questions or comments?

1-877-378-4249

Monday-Friday (9 a.m. - 5 p.m. EST)